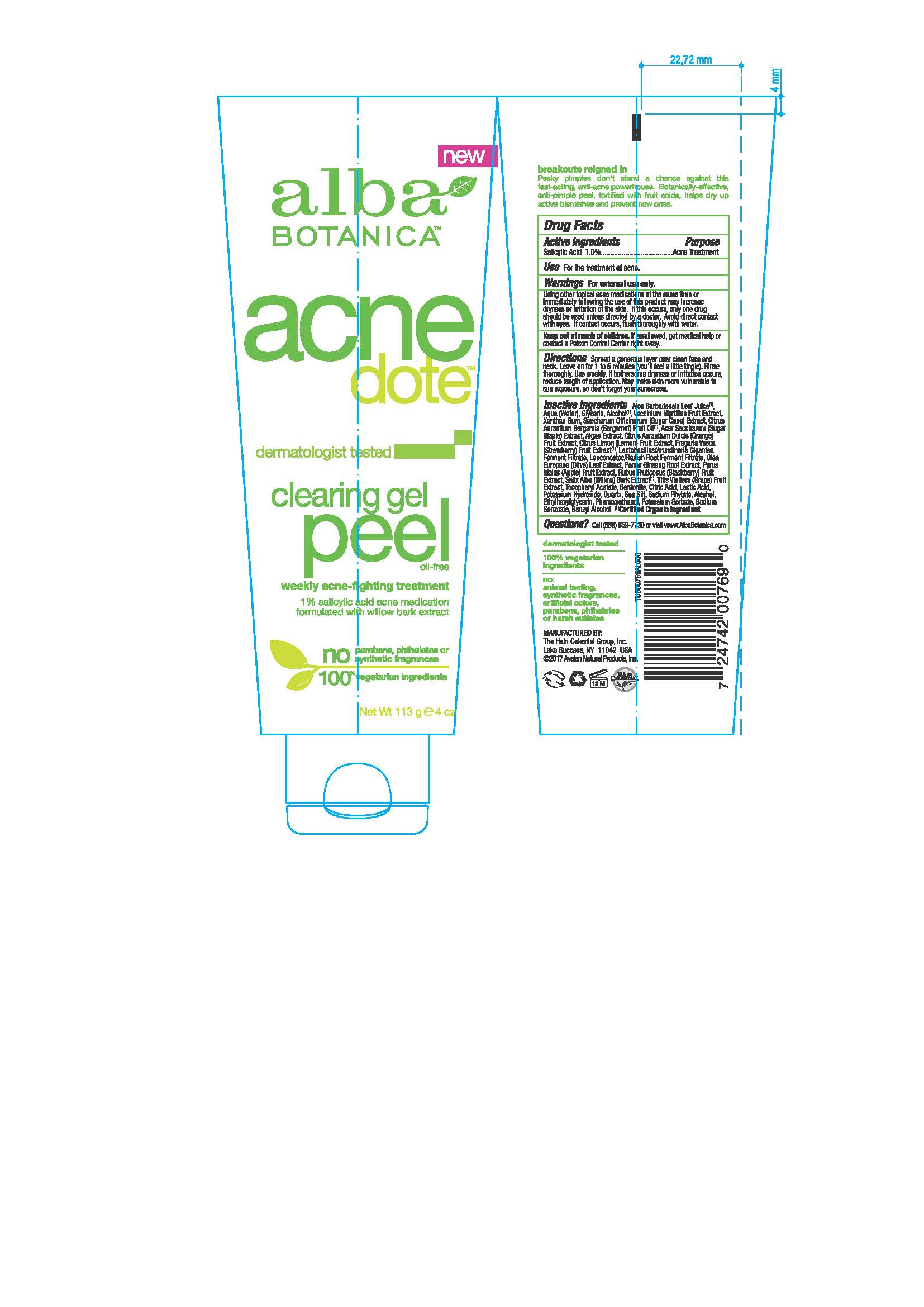 DRUG LABEL: AL0076900 Alba Botanica AcnedoteClearing Peel
NDC: 61995-2769 | Form: GEL
Manufacturer: The Hain Celestial Group, Inc.
Category: otc | Type: HUMAN OTC DRUG LABEL
Date: 20210412

ACTIVE INGREDIENTS: SALICYLIC ACID 1 g/100 g
INACTIVE INGREDIENTS: ALPINE STRAWBERRY; ASIAN GINSENG; APPLE; SALIX ALBA BARK; WINE GRAPE; LEMON; WATER; GLYCERIN; ACER SACCHARUM BARK/SAP; ALOE VERA LEAF; ORANGE; BLACKBERRY; SUGARCANE; CITRIC ACID MONOHYDRATE; ALCOHOL; PHENOXYETHANOL; POTASSIUM SORBATE; SODIUM BENZOATE; PHYTATE SODIUM; BERGAMOT OIL; LACTIC ACID; .ALPHA.-TOCOPHEROL ACETATE; BENTONITE; SEA SALT; OLEA EUROPAEA LEAF

Alba Botanica AcneDote Clearing Peel

Active Ingredient

Salicylic Acid 1.0%

DOSAGE AND ADMINISTRATION

Spread a generous layer over clean face and neck. Leave on for 1-5 minutes (you'll feel a little tingle). Rinse thoroughly. Use weekly.

PURPOSE

Acne Treatment

WARNINGS

Using other topical acne medications at the same time or immediately following the use of this product may increase dryness or irritation of the skin. If this occurs, only one drug should be used unless directed by a doctor. Avoid direct contact with eyes. If contact occurs, flush throughly with water.

Keep out of reach of children. If swallowed get medical help or contact Poison Center right away.

INACTIVE INGREDIENT

Aloe Barbadensis Leaf Juice(1), Water,Glycerin, Alcohol (1), Vaccinium Myrtillus Fruit Extract, Xanthan Gum, Saccharum Officinarum (Sugar Cane) Extract ,Citrus Aurantium Bergamia (Bergamot) Fruit Oil (1), Acer Saccharum (Sugar Maple) Extract, Algae Extract, Citrus Aurantium Dulcis (Orange) Fruit Extract, Citrus Limon (Lemon) Fruit Extract, Fragaria Vesca (Strawberry) Fruit Extract (1), Lactobacillus/Arundinaria Ferment Filtrate, Leuconostoc/Radish Root Ferment Filtrate, Olea Europaea (Olive) Leaf Extract, Panax Ginseng Root Extract, Purys Malus (Apple) Extract, Rubus Fruticosus (Blackberry) Fruit Extract, Salix Alba (Willow) Bark Extract (1), Vitis Vinifera(Grape) Fruit Extract, Citric Acid, Tocopheryl Acetate, Bentonite, Lactic Acid, Potassium Hydroxide, Quartz, Sea Salt, Sodium Phytate,Alcohol, Ethylhexylglycerine, Phenoxyethanol, Sodium Benzoate, Potassium Sorbate, BenzylAlcohol

(1) Certified Organicf Ingredient;

INDICATIONS AND USAGE

For the treatment of acne.